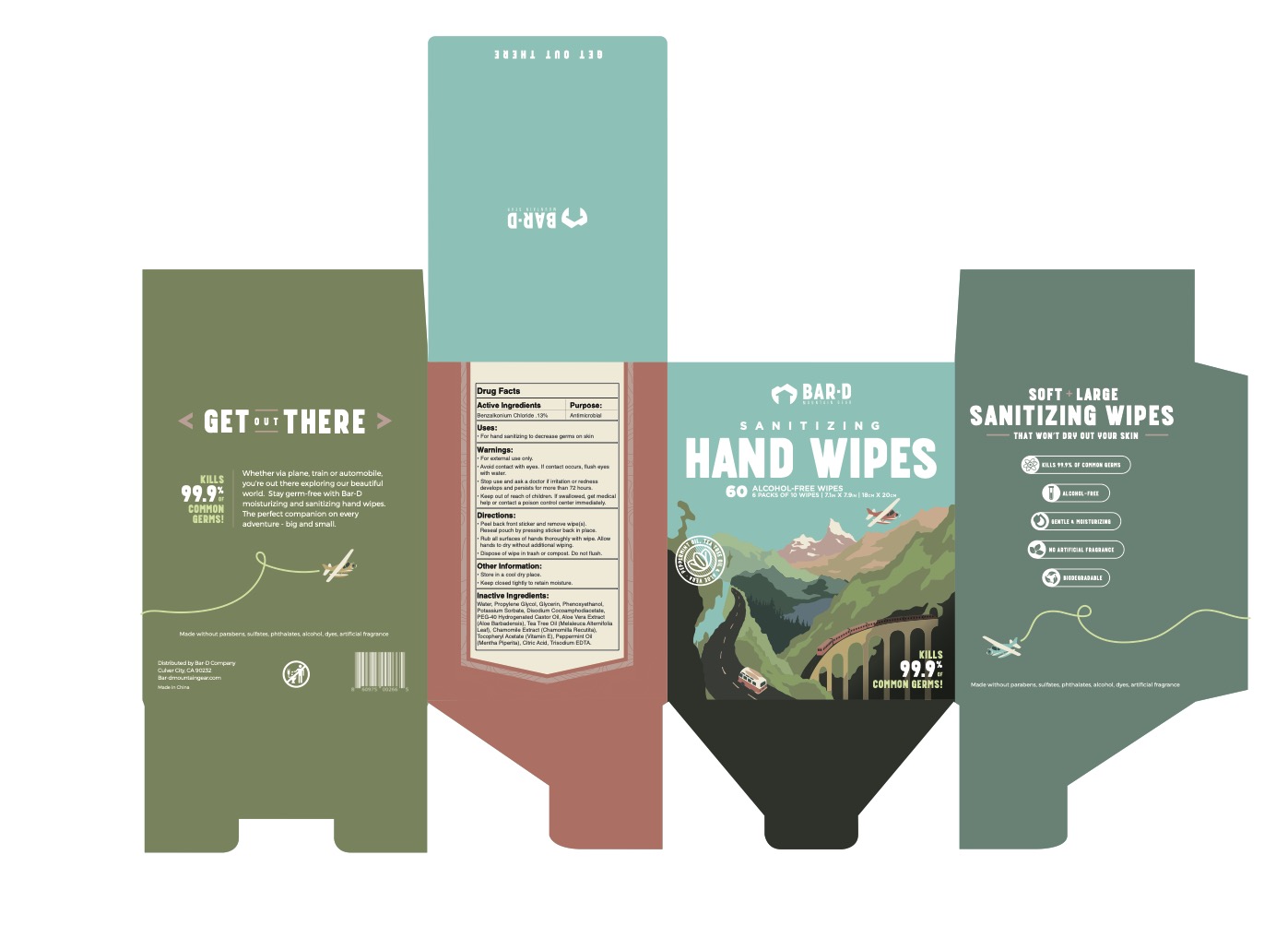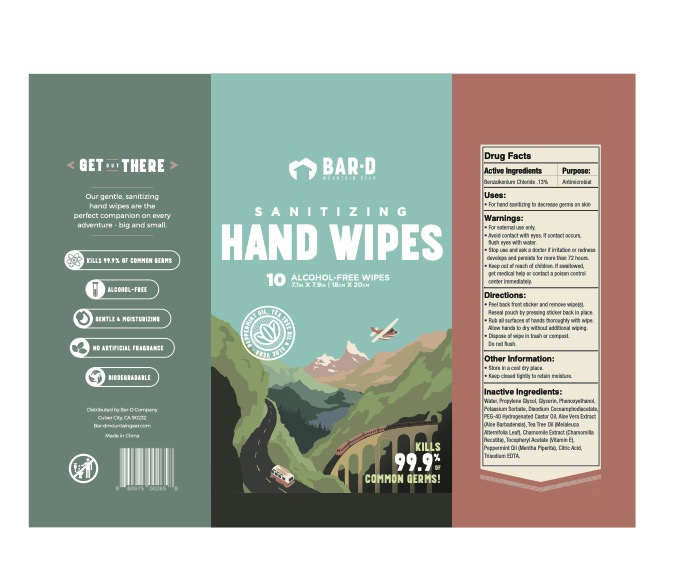 DRUG LABEL: Hand Sanitizing Wipes
NDC: 82303-001 | Form: CLOTH
Manufacturer: Bar-D Company
Category: otc | Type: HUMAN OTC DRUG LABEL
Date: 20221116

ACTIVE INGREDIENTS: BENZALKONIUM CHLORIDE 0.13 g/100 mL
INACTIVE INGREDIENTS: ALPHA-TOCOPHEROL ACETATE; CITRIC ACID MONOHYDRATE; POTASSIUM SORBATE; POLYOXYL 40 HYDROGENATED CASTOR OIL; GLYCERIN; TEA TREE OIL; WATER; DISODIUM COCOAMPHODIACETATE; PEPPERMINT OIL; PROPYLENE GLYCOL; ALOE VERA LEAF; PHENOXYETHANOL; CHAMOMILE; EDETATE TRISODIUM

Directions

- Peel back front sticker and remove wipe(s). Reseal pouch by pressing sticker back in place.
- Rub all surfaces of hands thoroughly with wipe. Allow hands to dry without additional wiping.
- Dispose of wipe in trash or compost. Do not flush.

Warnings

- For external use only.
- Avoid contact with eyes. If contact occurs, flush eyes with water.
- Stop use and ask a doctor if irritation or redness develops and persists for more than 72 hours.
- Keep out of reach of children. If swallowed, get medical help or contact a poison control center immediately

Uses

For hand sanitizing to decrase germs on skin.

Keep out of reach of children. If swallowed, get medical help or contact a poison control center immediately.

Purpose

Antimicrobial

Active Ingredients

Benzalkonium Chloride 0.13%

Purpose: Antimicrobial

Directions

Stop use and ask doctor if irritation or redness develops and persists for more than 72 hours.

Other Information

- Store in a cool dry place.
- Keep closed tightly to retain moisture.

Inactive Ingredients

Water, Propylene Glycol, Glycerin, Phenoxyethanol, Potassium Sorbate, Disodium Cocoamphodiacetate, PEG-40 Hydrogenated Castor Oil, Aloe Vera Extract (Aloe Barbadensis), Tea Tree Oil (Melaleuca Alternifolia Leaf), Chamomile Extract (Chamomilla Recutita), Tocopheryl Acetate (Vitamin E), Peppermint Oil (Mentha Piperita), Citric Acid, Trisodium EDTA